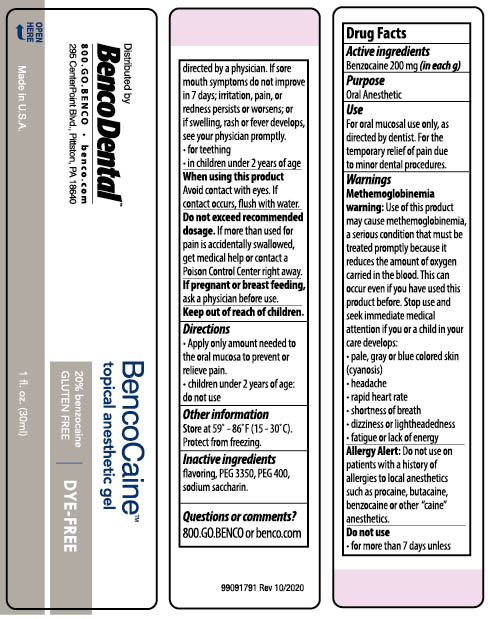 DRUG LABEL: BencoCaine Topical Anesthetic
NDC: 66975-341 | Form: GEL
Manufacturer: Benco Dental
Category: otc | Type: HUMAN OTC DRUG LABEL
Date: 20250108

ACTIVE INGREDIENTS: BENZOCAINE 200 mg/1 g
INACTIVE INGREDIENTS: POLYETHYLENE GLYCOL 3350; SACCHARIN SODIUM; POLYETHYLENE GLYCOL 400

Active Ingredients

Benzocaine 200 mg (in each g)

Purpose

Oral Anesthetic

INDICATIONS AND USAGE

For oral mucosal use only, as directed by dentist. For the temporary relif of pain due to minor dental procedures.

Warnings

Methemoglolllnemla
warning: Use of this product
may cause methemoglobinemia,
a seriouscondit~n that must be
treated promptly because tt
reduces the amount of oxygen
carried in the blood. This can
occur even if you have used this
product before. Stop use and
seek immediate medical
attention if you or a child in your
care develops:
• pale, gray or blue colored skin
(cyanosis)
•headache

- rapid heart rate

• shortness of breath
• dizziness or lightheadedness
• fatigue or lack of energy

Allergy Alert

Allergy Alert Do not use on
patients with a history of
allergies to local anesthetics
suchasprocaine,butacaine,
benzocaine or other "caine"
anesthetics.

Do not use

•for more than 7 days unless directed by a physician. If sore mouth symptoms do not improve in 7 days; irritation, pain, or redness persists or worsens; or worsens; or if swelling, rash or fever develops,see your physician promptly.
• for teething
•in children under 2 years of age

When using this product

Avoid contact with eyes. If contact occurs, flush with water.

Do not exceed recommended dosage

If more than used for pain is accidentally swallowed, get medical help or contact a Poison Control Center right away.

If pregnant or breast feeding,

ask a physician before use.

Directions

• Apply only amount needed to
the oral mucosa to prevent or
relieve pain.
• children under 2 years of age:
do not use

Other Information

Store at 59 -86°F(15-30°C).
Protect from freezing.

Inactive Ingredients

flavoring, PEG 3350, PEG 400, sodium saccharin.

Questions or Comments?

800.GO.BENCO or benco.com